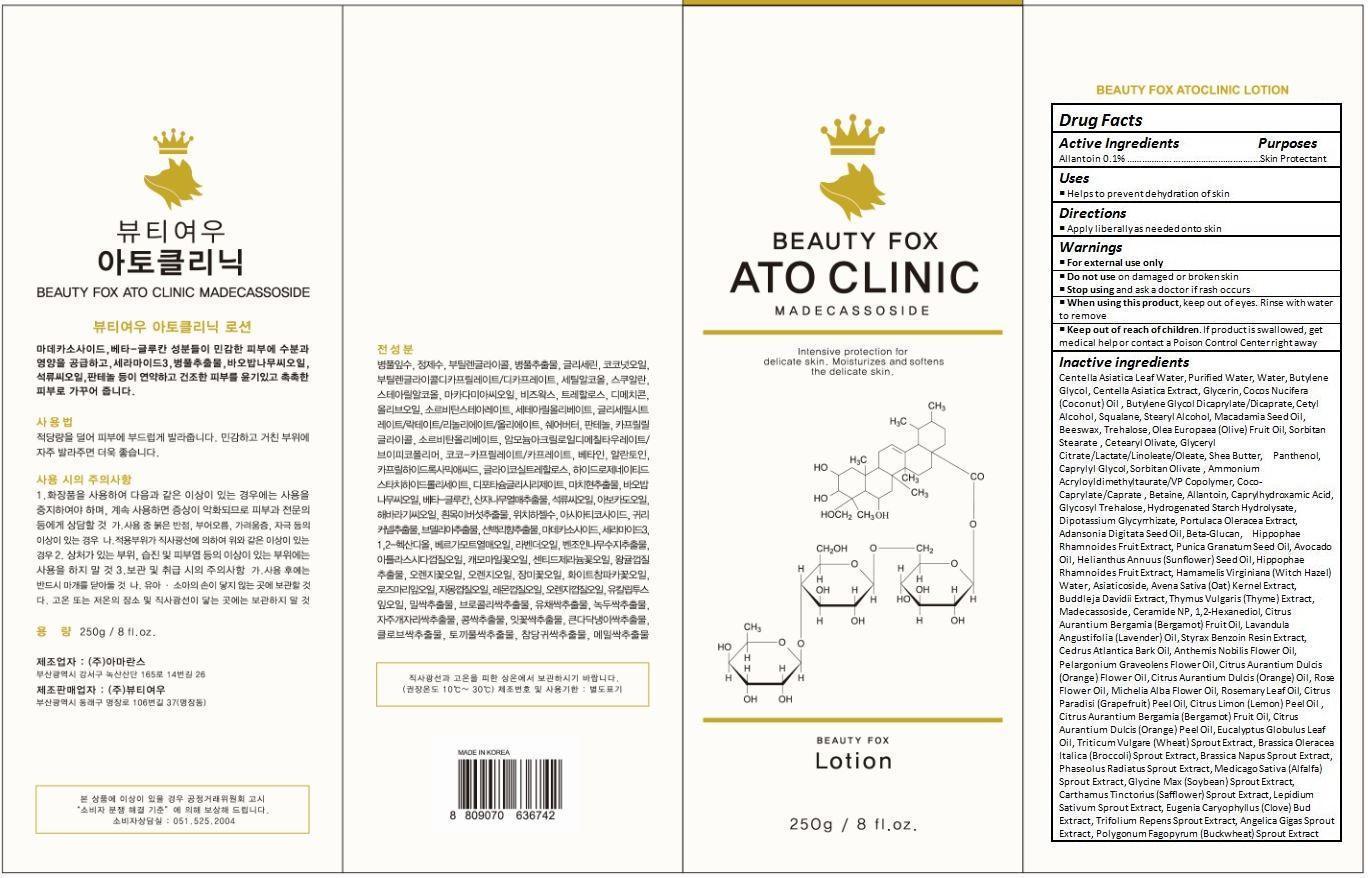 DRUG LABEL: BEAUTY FOX ATOCLINIC
NDC: 70129-002 | Form: LOTION
Manufacturer: Beauty Fox Co., Ltd.
Category: otc | Type: HUMAN OTC DRUG LABEL
Date: 20150930

ACTIVE INGREDIENTS: ALLANTOIN 0.25 g/250 g
INACTIVE INGREDIENTS: CENTELLA ASIATICA LEAF; WATER; BUTYLENE GLYCOL; CENTELLA ASIATICA; GLYCERIN; COCONUT OIL; BUTYLENE GLYCOL DICAPRYLATE/DICAPRATE; CETYL ALCOHOL; SQUALANE; STEARYL ALCOHOL; MACADAMIA OIL; YELLOW WAX; TREHALOSE; DIMETHICONE; OLIVE OIL; SORBITAN OLIVATE; CETEARYL OLIVATE; SHEA BUTTER; PANTHENOL; CAPRYLYL GLYCOL; AMMONIUM ACRYLOYLDIMETHYLTAURATE/VP COPOLYMER; COCO-CAPRYLATE/CAPRATE; BETAINE; CAPRYLHYDROXAMIC ACID; HYDROGENATED STARCH HYDROLYSATE; GLYCYRRHIZINATE DIPOTASSIUM; PURSLANE; ADANSONIA DIGITATA SEED OIL; CURDLAN; HIPPOPHAE RHAMNOIDES FRUIT; POMEGRANATE SEED OIL; AVOCADO OIL; SUNFLOWER OIL; HAMAMELIS VIRGINIANA TOP WATER; ASIATICOSIDE; OAT; THYME; MADECASSOSIDE; CERAMIDE NP; 1,2-HEXANEDIOL; BERGAMOT OIL; LAVENDER OIL; STYRAX BENZOIN RESIN; CEDRUS ATLANTICA BARK OIL; CHAMAEMELUM NOBILE FLOWER OIL; PELARGONIUM GRAVEOLENS FLOWER OIL; CITRUS SINENSIS FLOWER OIL; ORANGE OIL; ROSA RUGOSA FLOWER BUD; MAGNOLIA X ALBA FLOWER OIL; ROSEMARY OIL; GRAPEFRUIT OIL; LEMON OIL; EUCALYPTUS OIL; WHEAT SPROUT; BROCCOLI SPROUT; BEAN SPROUT; ALFALFA TOP; SOYBEAN; SAFFLOWER; GARDEN CRESS SPROUT; CLOVE; ANGELICA GIGAS ROOT; BUCKWHEAT

Drug Facts

ACTIVE INGREDIENT

ALLANTOIN 0.10%

PURPOSE

Skin Protectant

INDICATIONS AND USAGE

Helps to prevent dehydration of skin

DOSAGE AND ADMINISTRATION

Apply liberally as needed onto skin

WARNINGS

For external use only.
Do not use on damaged or broken skin.
When using this product, keep out of eyes. Rinse with water to remove.
Stop using and ask a doctor if rash occurs.

KEEP OUT OF REACH OF CHILDREN

Keep out of reach of the children. If product is swallowed, get medical help or contact a poison control center right away.

INACTIVE INGREDIENT

Centella Asiatica Leaf Water, Purified Water, Water, Butylene Glycol, Centella Asiatica Extract, Glycerin, Cocos Nucifera (Coconut) Oil , Butylene Glycol Dicaprylate/Dicaprate, Cetyl Alcohol, Squalane, Stearyl Alcohol, Macadamia Seed Oil, Beeswax, Trehalose, Olea Europaea (Olive) Fruit Oil, Sorbitan Stearate , Cetearyl Olivate, Glyceryl Citrate/Lactate/Linoleate/Oleate, Shea Butter, Panthenol, Caprylyl Glycol, Sorbitan Olivate , Ammonium Acryloyldimethyltaurate/VP Copolymer, Coco-Caprylate/Caprate , Betaine, Allantoin, Caprylhydroxamic Acid, Glycosyl Trehalose, Hydrogenated Starch Hydrolysate, Dipotassium Glycyrrhizate, Portulaca Oleracea Extract, Adansonia Digitata Seed Oil, Beta-Glucan, Hippophae Rhamnoides Fruit Extract, Punica Granatum Seed Oil, Avocado Oil, Helianthus Annuus (Sunflower) Seed Oil, Hippophae Rhamnoides Fruit Extract, Hamamelis Virginiana (Witch Hazel) Water, Asiaticoside, Avena Sativa (Oat) Kernel Extract, Buddleja Davidii Extract, Thymus Vulgaris (Thyme) Extract, Madecassoside, Ceramide NP, 1,2-Hexanediol, Citrus Aurantium Bergamia (Bergamot) Fruit Oil, Lavandula Angustifolia (Lavender) Oil, Styrax Benzoin Resin Extract, Cedrus Atlantica Bark Oil, Anthemis Nobilis Flower Oil, Pelargonium Graveolens Flower Oil, Citrus Aurantium Dulcis (Orange) Flower Oil, Citrus Aurantium Dulcis (Orange) Oil, Rose Flower Oil, Michelia Alba Flower Oil, Rosemary Leaf Oil, Citrus Paradisi (Grapefruit) Peel Oil, Citrus Limon (Lemon) Peel Oil , Citrus Aurantium Bergamia (Bergamot) Fruit Oil, Citrus Aurantium Dulcis (Orange) Peel Oil, Eucalyptus Globulus Leaf Oil, Triticum Vulgare (Wheat) Sprout Extract, Brassica Oleracea Italica (Broccoli) Sprout Extract, Brassica Napus Sprout Extract, Phaseolus Radiatus Sprout Extract, Medicago Sativa (Alfalfa) Sprout Extract, Glycine Max (Soybean) Sprout Extract, Carthamus Tinctorius (Safflower) Sprout Extract, Lepidium Sativum Sprout Extract, Eugenia Caryophyllus (Clove) Bud Extract, Trifolium Repens Sprout Extract, Angelica Gigas Sprout Extract, Polygonum Fagopyrum (Buckwheat) Sprout Extract